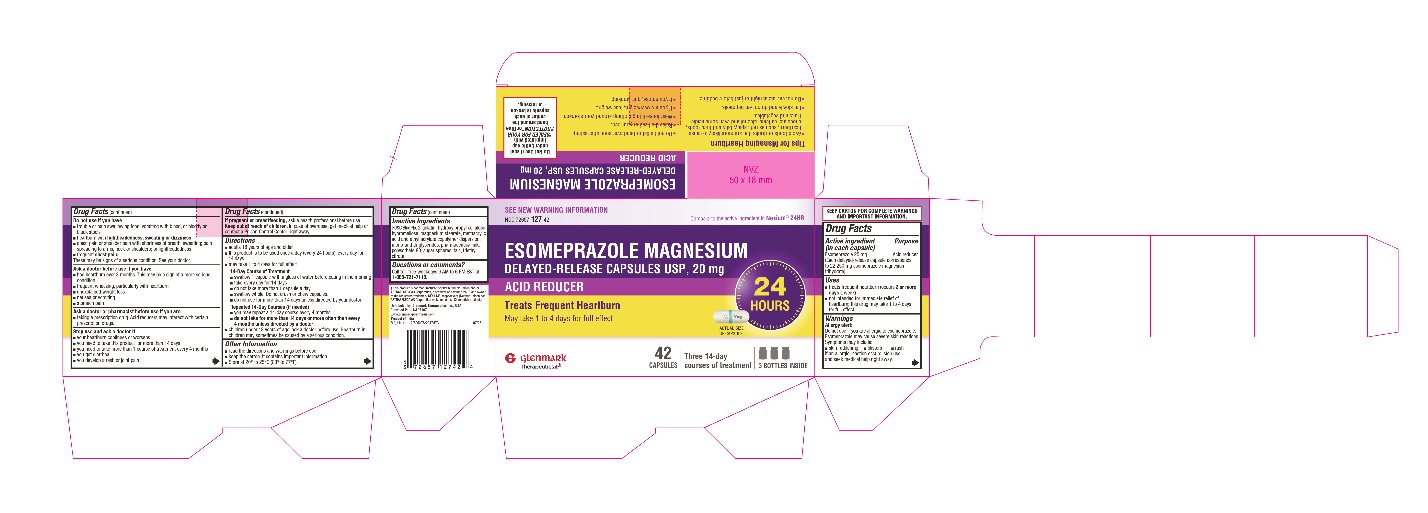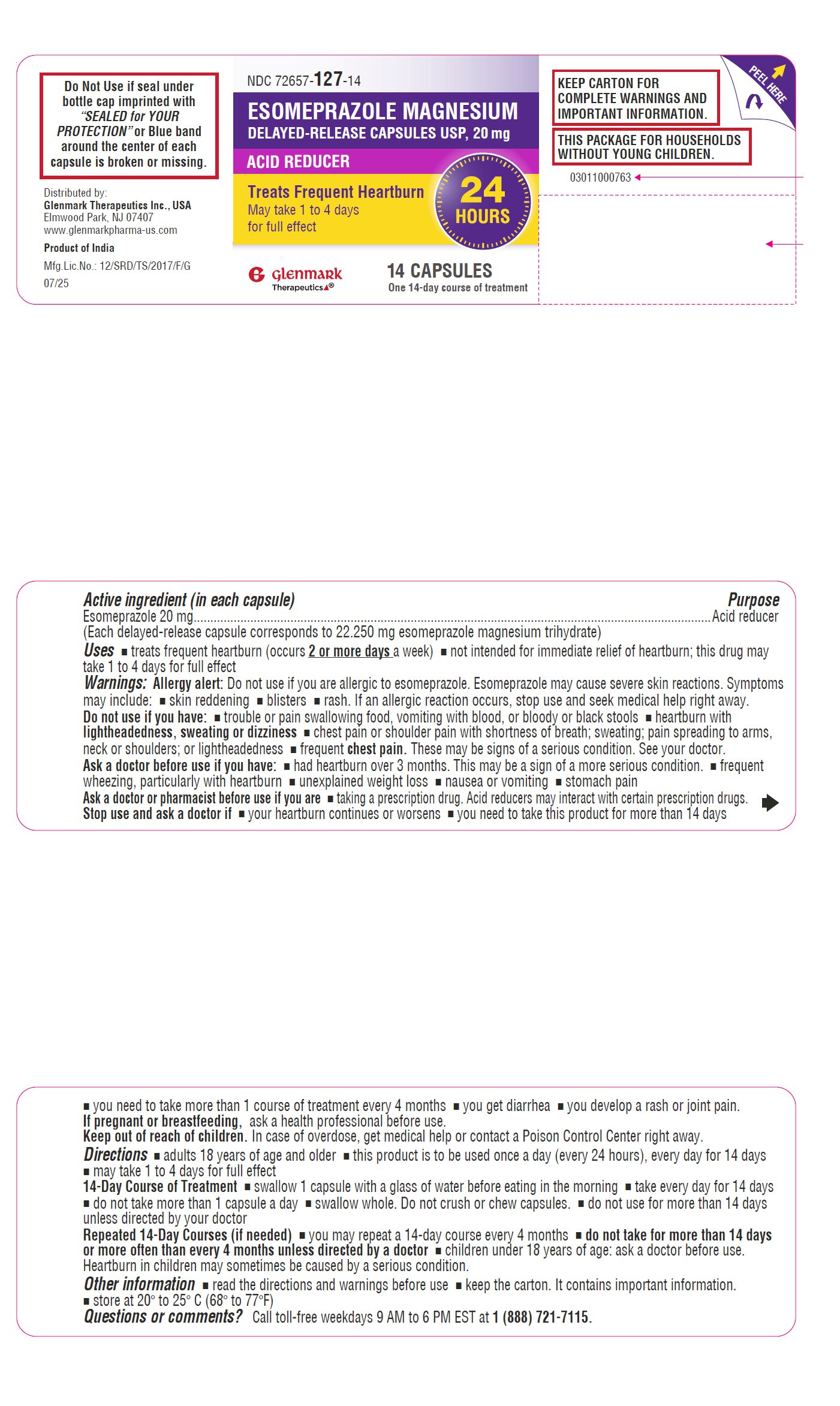 DRUG LABEL: esomeprazole magnesium
NDC: 72657-127 | Form: CAPSULE, DELAYED RELEASE
Manufacturer: GLENMARK THERAPEUTICS INC., USA
Category: otc | Type: HUMAN OTC DRUG LABEL
Date: 20260123

ACTIVE INGREDIENTS: ESOMEPRAZOLE MAGNESIUM TRIHYDRATE 20 mg/1 1
INACTIVE INGREDIENTS: RAW SUGAR; HYPROMELLOSE 2910 (5 MPA.S); POLYSORBATE 80; HYDROXYPROPYL CELLULOSE, UNSPECIFIED; TALC; MAGNESIUM STEARATE; METHACRYLIC ACID AND ETHYL ACRYLATE COPOLYMER; TRIETHYL CITRATE; GELATIN, UNSPECIFIED; FD&C BLUE NO. 2; GLYCERYL MONOSTEARATE; GLYCERYL DISTEARATE

Esomeprazole Magnesium Delayed-Release Capsules USP, 20 mg Drug Facts

Active ingredient

Esomeprazole 20 mg

(Each delayed-release capsule corresponds to 22.250 mg esomeprazole magnesium trihydrate)

Purpose

Acid reducer

Keep out of reach of children. In case of overdose, get medical help or contact a Poison Control Center right away.

Uses

- treats frequent heartburn (occurs 2 or more days a week)
- not intended for immediate relief of heartburn; this drug may take 1 to 4 days for full effect

Warnings

Allergy alert:

Do not use if you are allergic to esomeprazole.

Esomeprazole may cause severe skin reactions.

Symptoms may include:

- skin reddening
- blisters
- rash

If an allergic reaction occurs, stop use and seek medical help right away.

Do not use if you have

- trouble or pain swallowing food, vomiting with blood, or bloody or black stools
- heartburn with lightheadedness , sweating or dizziness
- chest pain or shoulder pain with shortness of breath; sweating; pain spreading to arms, neck or shoulders; or lightheadedness
- frequent chest pain

These may be signs of a serious condition. See your doctor.

Ask a doctor before use if you have

- had heartburn over 3 months. This may be a sign of a more serious condition.
- frequent wheezing, particularly with heartburn
- unexplained weight loss
- nausea or vomiting
- stomach pain

Ask a doctor or pharmacist before use if you are

- taking a prescription drug. Acid reducers may interact with certain prescription drugs.

Stop use and ask a doctor if

- your heartburn continues or worsens
- you need to take this product for more than 14 days
- you need to take more than 1 course of treatment every 4 months
- you get diarrhea
- you develop a rash or joint pain

If pregnant or breast-feeding, ask a health professional before use.

Directions

- adults 18 years of age and older
- this product is to be used once a day (every 24 hours), every day for 14 days
- may take 1 to 4 days for full effect

14-Day Course of Treatment

- swallow 1 capsule with a glass of water before eating in the morning
- take every day for 14 days
- do not take more than 1 capsule a day
- swallow whole. Do not crush or chew capsules.
- do not use for more than 14 days unless directed by your doctor

Repeated 14-Day Courses (if needed)

- you may repeat a 14-day course every 4 months
- do not take for more than 14 days or more often than every 4 months unless directed by a doctor
- children under 18 years of age: ask a doctor before use. Heartburn in children may sometimes be caused by a serious condition.

Other Information

- read the directions and warnings before use
- keep the carton. It contains important information.
- Store at 20° to 25°C (68° to 77°F).

Questions or comments?

Call toll-free weekdays 9 AM to 6 PM EST at 1-888-721-7115.

Product of India

Additional Information

Do Not Use if seal under bottle cap imprinted with "SEALED for YOUR PROTECTION" or Blue band around the center of each capsule is broken or missing.

Tips for Managing Heartburn

- Avoid foods or drinks that are more likely to cause heartburn, such as rich, spicy, fatty and fried foods, chocolate, caffeine, alcohol and even some acidic fruits and vegetables.
- Eat slowly and do not eat big meals.
- Do not eat late at night or just before bedtime.
- Do not lie flat or bend over soon after eating.
- Raise the head of your bed.
- Wear loose-fitting clothing around your stomach.
- If you are overweight, lose weight.
- If you smoke, quit smoking.

Distributed by:

Glenmark Therapeutics Inc., USA

Elmwood Park, NJ 07407

Product of India

07/25

Inactive Ingredients

FD&C Blue No. 2, gelatin, hydroxy propyl cellulose, hypromellose, magnesium stearate, methacrylic

acid and ethyl acrylate copolymer dispersion, mono-and di-glycerides, pharmaceutical ink, polysorbate 80, sugar spheres, talc, triethyl citrate.

Package/Label Principal Display Panel

Principal Display Panel - 20 mg Capsules: Container Label

NDC 72657-127-14

Esomeprazole Magnesium Delayed-Release Capsules USP, 20 mg

Acid Reducer

Treats Frequent Heartburn

May take 1 to 4 days for full effect

24 HOURS

14 Capsules

One 14-day course of treatment

Product of India

Package/Label Principal Display Panel

Principal Display Panel - 42 Capsules Carton label

NDC 73657-127-42

Esomeprazole Magnesium Delayed-Release Capsules USP, 20 mg

Acid Reducer

Treats Frequent Heartburn

May take 1 to 4 days for full effect

24 HOURS

42 Capsules

Three 14-day courses of treatment

Product of India